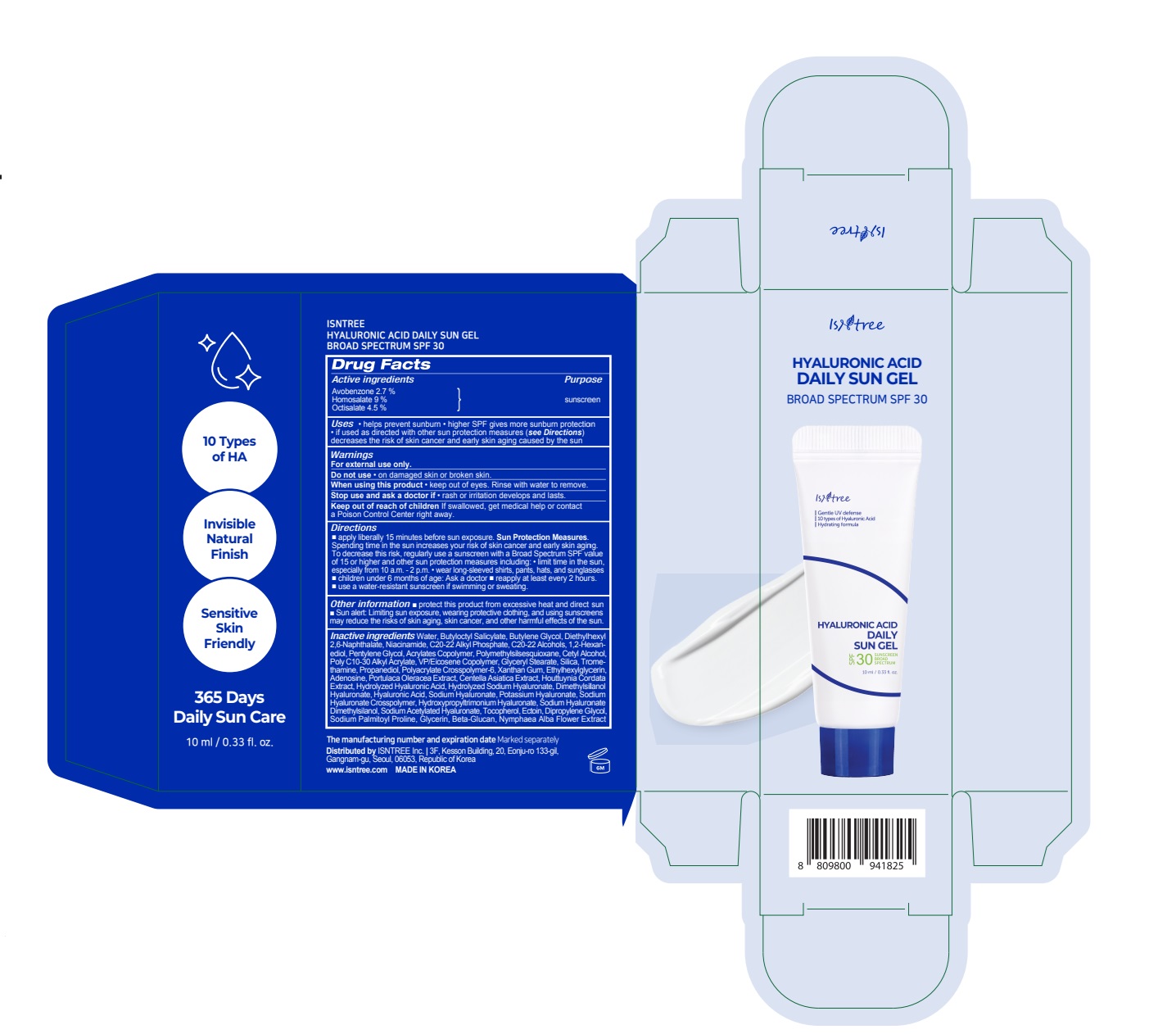 DRUG LABEL: ISNTREE HYALURONIC ACID DAILY SUNGEL
NDC: 81100-103 | Form: CREAM
Manufacturer: ISNTREE Inc.
Category: otc | Type: HUMAN OTC DRUG LABEL
Date: 20250109

ACTIVE INGREDIENTS: HOMOSALATE 0.9 g/10 mL; AVOBENZONE 0.27 g/10 mL; OCTISALATE 0.45 g/10 mL
INACTIVE INGREDIENTS: POLYMETHYLSILSESQUIOXANE (4.5 MICRONS); XANTHAN GUM; ADENOSINE; DIETHYLHEXYL 2,6-NAPHTHALATE; NIACINAMIDE; CETYL ALCOHOL; SILICON DIOXIDE; PROPANEDIOL; HYALURONIC ACID; SODIUM PALMITOYL PROLINE; GLYCERIN; ETHYLHEXYLGLYCERIN; SODIUM ACETYLATED HYALURONATE; BUTYLENE GLYCOL; DIMETHYLSILANOL HYALURONATE; HYALURONATE SODIUM; C20-22 ALCOHOLS; TOCOPHEROL; DIPROPYLENE GLYCOL; PENTYLENE GLYCOL; TROMETHAMINE; CENTELLA ASIATICA TRITERPENOIDS; HOUTTUYNIA CORDATA FLOWERING TOP; PURSLANE; ECTOINE; WATER; GLYCERYL MONOSTEARATE; AMMONIUM ACRYLOYLDIMETHYLTAURATE, DIMETHYLACRYLAMIDE, LAURYL METHACRYLATE AND LAURETH-4 METHACRYLATE COPOLYMER, TRIMETHYLOLPROPANE TRIACRYLATE CROSSLINKED (45000 MPA.S); NYMPHAEA ALBA FLOWER; BUTYLOCTYL SALICYLATE; C20-22 ALKYL PHOSPHATE; 1,2-HEXANEDIOL

ISNTREE HYALURONIC ACID DAILY SUN GEL 10 mL

Active ingredients

Avobenzone 2.7 %
Homosalate 9 %
Octisalate 4.5 %

Purpose

sunscreen

Uses

• helps prevent sunburn • higher SPF gives more sunburn protection
• if used as directed with other sun protection measures (see Directions)
decreases the risk of skin cancer and early skin aging caused by the sun

Warnings

For external use only.

Do not use

• on damaged skin or broken skin.

When using this product

• keep out of eyes. Rinse with water to remove.

Stop use and ask a doctor if

•rash or irritation develops and lasts.

Keep out of reach of children

If swallowed, get medical help or contact
a Poison Control Center right away.

Directions

■ apply liberally 15 minutes before sun exposure.
Sun Protection Measures. Spending time in the sun increases your risk of
skin cancer and early skin aging. To decrease this risk, regularly use a
sunscreen with a Broad Spectrum SPF value of 15 or higher and other
sun protection measures including:
• limit time in the sun, especially from 10 a.m. - 2 p.m.
• wear long-sleeved shirts, pants, hats, and sunglasses
■ children under 6 months of age: Ask a doctor
■ reapply at least every 2 hours.
■ use a water-resistant sunscreen if swimming or sweating.

Other information

■ protect the product from exessive heat and
direct sun ■ Sun alert: Limiting sun exposure, wearing protective clothing, and
using sunscreens may reduce the risks of skin aging, skin cancer, and other
harmful effects of the sun.

Inactive ingredients

Water, Butyloctyl Salicylate, Butylene Glycol, Diethylhexyl 2,6-Naphthalate, Niacinamide, C20-22 Alkyl Phosphate, C20-22 Alcohols, 1,2-Hexanediol, Pentylene Glycol, Acrylates Copolymer, Polymethylsilsesquioxane, Cetyl Alcohol, Poly C10-30 Alkyl Acrylate, VP/Eicosene Copolymer, Glyceryl Stearate, Silica, Tromethamine, Propanediol, Polyacrylate Crosspolymer-6, Xanthan Gum, Ethylhexylglycerin, Adenosine, Portulaca Oleracea Extract, Centella Asiatica Extract, Houttuynia Cordata Extract, Hydrolyzed Hyaluronic Acid, Hydrolyzed Sodium Hyaluronate, Dimethylsilanol Hyaluronate, Hyaluronic Acid, Sodium Hyaluronate, Potassium Hyaluronate, Sodium Hyaluronate Crosspolymer, Hydroxypropyltrimonium Hyaluronate, Sodium Hyaluronate Dimethylsilanol, Sodium Acetylated Hyaluronate, Tocopherol, Ectoin, Dipropylene Glycol, Sodium Palmitoyl Proline, Glycerin, Beta-Glucan, Nymphaea Alba Flower Extract